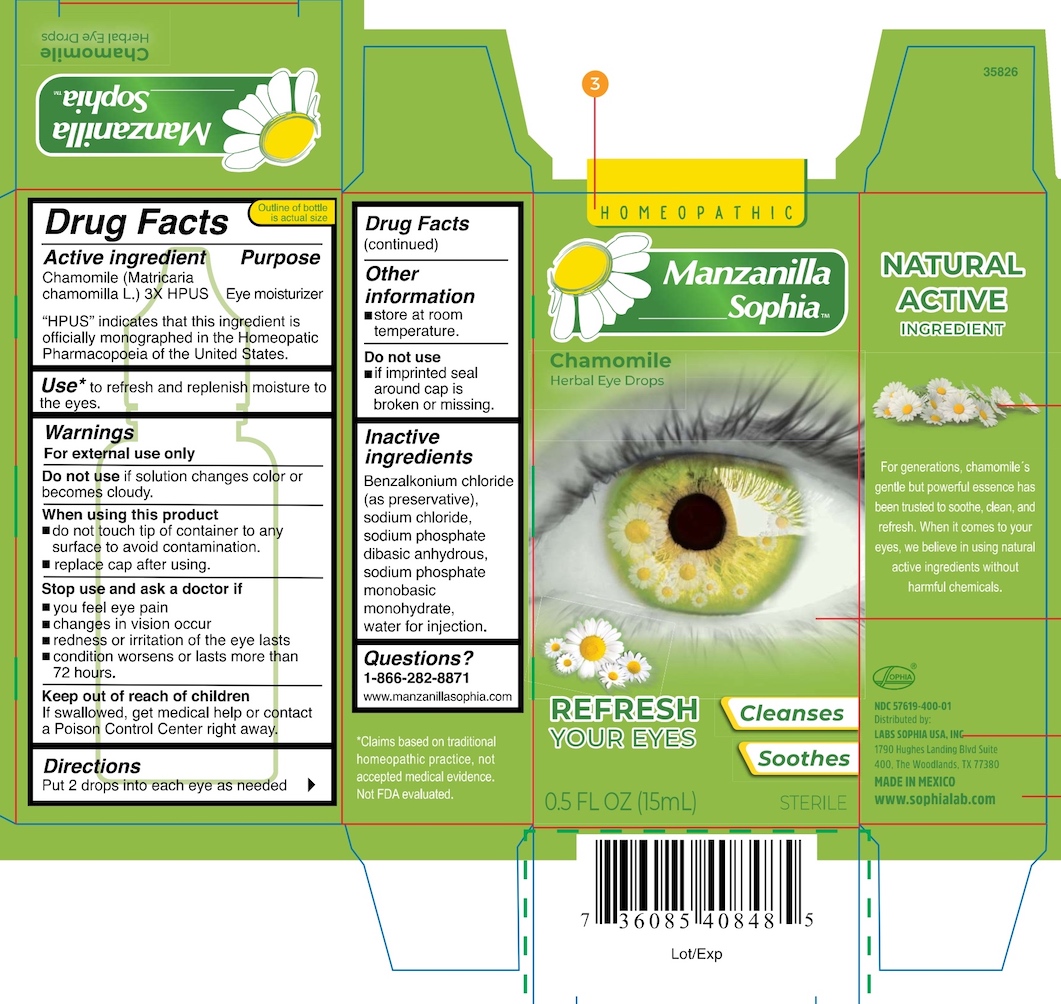 DRUG LABEL: Manzanilla
NDC: 57619-400 | Form: SOLUTION/ DROPS
Manufacturer: LABORATORIOS SOPHIA, S.A. DE C.V.
Category: homeopathic | Type: HUMAN OTC DRUG LABEL
Date: 20240109

ACTIVE INGREDIENTS: MATRICARIA RECUTITA 3 [hp_X]/1 mL
INACTIVE INGREDIENTS: BENZALKONIUM CHLORIDE; WATER; SODIUM CHLORIDE; SODIUM PHOSPHATE, MONOBASIC, MONOHYDRATE; SODIUM PHOSPHATE, DIBASIC, ANHYDROUS

Manzanilla Sophia Herbal Eye Drops

Drug Facts

Active ingredient

Chamomile (Matricaria chamomilla L.) 3X HPUS

"HPUS" indicates that this ingredient is officially monographed in the Homeopathic Pharmacopoeia of the United States.

Purpose

Eye moisturizer

INDICATIONS AND USAGE

Use* to refresh and replenish moisture to eyes.

Warnings

For external use only

Do not use if solution changes color or becomes cloudy

When using this product

- do not touch tip of container to any surface to avoid contamination
- replace cap after using

Stop use and ask a doctor if

- you feel eye pain
- changes in vision occur
- redness or irritation of the eye lasts
- condition worsens or lasts more than 72 hours

Keep out of reach of children. If swallowed, get medical help or contact a Poison Control Center right away

Directions

Put 2 drops into each eye as needed

Other information

- store at room temperature.

Do not use

- if imprinted seal around cap is broken or missing

INACTIVE INGREDIENT

Inactive ingredients Benzalkonium chloride (as preservative), sodium chloride, sodium phosphate dibasic monohydrate, sodium phosphate monobasic monohydrate, water for injection

Questions?

1-866-202-8871

www.manzanillasophia.com

*Claims based on traditional homeopathic practice, not accepted medical evidence. Not FDA evaluated.

NDC 57619-400-01

Distributed by:

LABS SOPHIA USA, INC.

1790 Hughes Landing Blvd Suite 400

The Woodlands, TX 77380

MADE IN MEXICO

www.sophialabs.com

PACKAGE LABEL

HOMEOPATHIC

Manzanilla Sophia™

Chamomile

Herbal Eye Drops

REFRESH YOUR EYES

Cleanses

Soothes

0.5 FL OZ (15 mL)

STERILE